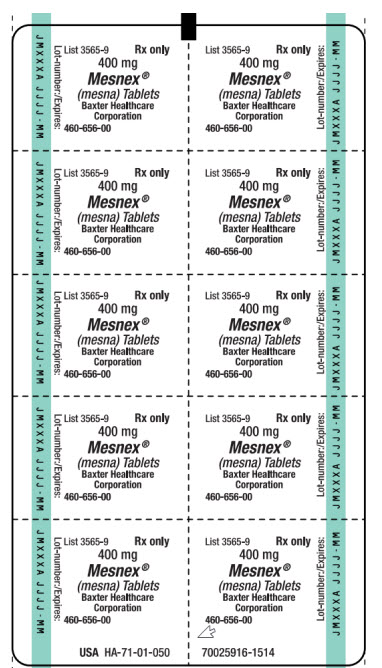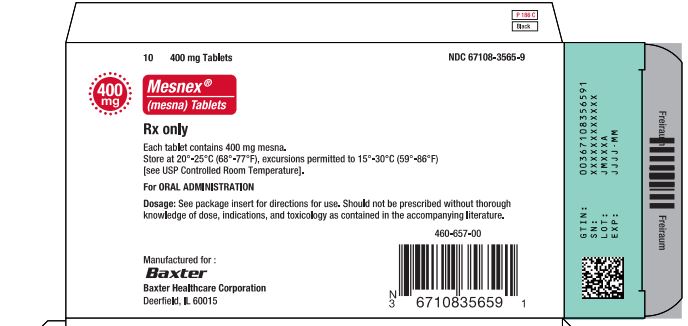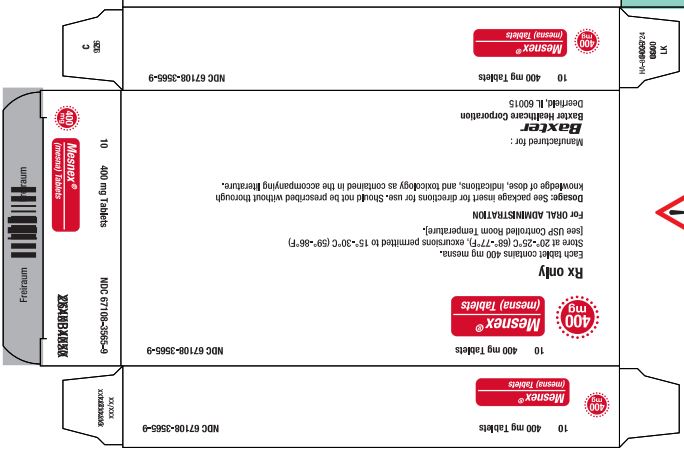 DRUG LABEL: MESNEX
NDC: 67108-3565 | Form: TABLET, FILM COATED
Manufacturer: Baxter Healthcare Company
Category: prescription | Type: HUMAN PRESCRIPTION DRUG LABEL
Date: 20191221

ACTIVE INGREDIENTS: MESNA 400 mg/1 1
INACTIVE INGREDIENTS: LACTOSE; CELLULOSE, MICROCRYSTALLINE; CALCIUM PHOSPHATE, DIBASIC, DIHYDRATE; STARCH, CORN; POVIDONE, UNSPECIFIED; MAGNESIUM STEARATE; HYDROXYPROPYL CELLULOSE (1600000 WAMW); POLYETHYLENE GLYCOL, UNSPECIFIED; TITANIUM DIOXIDE; DIMETHICONE

HIGHLIGHTS OF PRESCRIBING INFORMATION

These highlights do not include all the information needed to use MESNEX safely and effectively. See full prescribing information for MESNEX.
MESNEX (mesna) tablets, for oral use
MESNEX (mesna) injection, for intravenous use
Initial U.S. Approval: 1988

RECENT MAJOR CHANGES

Warnings and Precautions, Benzyl Alcohol Toxicity (5.3) 12/2018

1 INDICATIONS AND USAGE

MESNEX is a cytoprotective agent indicated as a prophylactic agent in reducing the incidence of ifosfamide-induced hemorrhagic cystitis. (1)

Limitation of Use:

MESNEX is not indicated to reduce the risk of hematuria due to other pathological conditions such as thrombocytopenia. (1)

2 DOSAGE AND ADMINISTRATION

MESNEX may be given on a fractionated dosing schedule of three bolus intravenous injections or a single bolus injection followed by two oral administrations of MESNEX tablets as outlined below. The dosing schedule should be repeated on each day that ifosfamide is administered. When the dosage of ifosfamide is adjusted, the ratio of MESNEX to ifosfamide should be maintained. (2)

Intravenous Dosing Schedule:
 | 0 Hours | 4 Hours | 8 Hours
Ifosfamide | 1.2 g/m^2 | -- | --
MESNEX injection | 240 mg/m^2 | 240 mg/m^2 | 240 mg/m^2

Intravenous and Oral Dosing Schedule:
 | 0 Hours | 2 Hours | 6 Hours
Ifosfamide | 1.2 g/m^2 | -- | --
MESNEX injection | 240 mg/m^2 | -- | --
MESNEX tablets | -- | 480 mg/m^2 | 480 mg/m^2

Maintain sufficient urinary output, as required for ifosfamide treatment, and monitor urine for the presence of hematuria. (2.3)

3 DOSAGE FORMS AND STRENGTHS

1. Injection: 1g (100 mg/mL) Multidose vials (3)
2. Tablets: 400 mg with functional score (3)

4 CONTRAINDICATIONS

- Known hypersensitivity to mesna or to any of the excipients in MESNEX, including benzyl alcohol. (4)

5 WARNINGS AND PRECAUTIONS

1. Hypersensitivity reactions: Anaphylactic reactions have been reported. Less severe hypersensitivity reactions may also occur. Monitor patients. If a reaction occurs, discontinue MESNEX and provide supportive care. (5.1)
2. Dermatologic toxicity: Skin rash with eosinophilia and systemic symptoms, Stevens-Johnson syndrome, and toxic epidermal necrolysis have occurred. Skin rash, urticaria, and angioedema have also been seen. Monitor patients. If a reaction occurs, discontinue MESNEX and provide supportive care. (5.2)
3. Benzyl alcohol toxicity: Serious and fatal adverse reactions can occur in premature neonates and low-birth weight infants treated with benzyl alcohol-preserved drugs, including MESNEX injection. Avoid use in premature neonates and low-birth weight infants. (5.3)
4. Laboratory test alterations: False positive tests for urinary ketones and interference with enzymatic CPK activity tests have been seen. (5.4)

6 ADVERSE REACTIONS

The most common adverse reactions (> 10%) when MESNEX is given with ifosfamide are nausea, vomiting, constipation, leukopenia, fatigue, fever, anorexia, thrombocytopenia, anemia, granulocytopenia, diarrhea, asthenia, abdominal pain, headache, alopecia, and somnolence. (6.1)

To report SUSPECTED ADVERSE REACTIONS, contact Baxter Healthcare at 1-866-888-2472, or FDA at 1-800-FDA-1088 or www.fda.gov/medwatch.

8 USE IN SPECIFIC POPULATIONS

1. Pregnancy: MESNEX in combination with ifosfamide can cause fetal harm. Advise patients of potential risk to a fetus. (8.1)
2. Lactation: Do not breastfeed. (8.2)
3. Females and Males of Reproductive Potential: Advise patients to use effective contraception. Verify pregnancy status prior to initiation of MESNEX in combination with ifosfamide. (8.3)
4. Pediatric use: In premature neonates and low-birth weight infants, avoid use of benzyl alcohol–containing solutions. (8.4)
5. Geriatric use: Dose selection should be cautious. (8.5)

FULL PRESCRIBING INFORMATION

1 INDICATIONS AND USAGE

MESNEX is indicated as a prophylactic agent in reducing the incidence of ifosfamide-induced hemorrhagic cystitis.

Limitation of Use:

MESNEX is not indicated to reduce the risk of hematuria due to other pathological conditions such as thrombocytopenia.

2 DOSAGE AND ADMINISTRATION

2.1 Intravenous Dosing

MESNEX may be given on a fractionated dosing schedule of three bolus intravenous injections as outlined below.

MESNEX injection is given as intravenous bolus injections in a dosage equal to 20% of the ifosfamide dosage weight by weight (w/w) at the time of ifosfamide administration and 4 and 8 hours after each dose of ifosfamide. The total daily dose of MESNEX is 60% of the ifosfamide dose. The recommended dosing schedule is outlined below in Table 1.

Table 1. Recommended Intravenous Dosing Schedule
 | 0 Hours | 4 Hours | 8 Hours
Ifosfamide | 1.2 g/m^2 | – | –
MESNEX injection [The dosing schedule should be repeated on each day that ifosfamide is administered. When the dosage of ifosfamide is increased or decreased, the ratio of MESNEX to ifosfamide should be maintained.] | 240 mg/m^2 | 240 mg/m^2 | 240 mg/m^2

2.2 Intravenous and Oral Dosing

MESNEX may be given on a fractionated dosing schedule of a single bolus injection followed by two oral administrations of MESNEX tablets as outlined below.

MESNEX injection is given as intravenous bolus injections in a dosage equal to 20% of the ifosfamide dosage (w/w) at the time of ifosfamide administration. MESNEX tablets are given orally in a dosage equal to 40% of the ifosfamide dose 2 and 6 hours after each dose of ifosfamide. The total daily dose of MESNEX is 100% of the ifosfamide dose. The recommended dosing schedule is outlined in Table 2.

Table 2. Recommended Intravenous and Oral Dosing Schedule
 | 0 Hours | 2 Hours | 6 Hours
Ifosfamide | 1.2 g/m^2 | – | –
MESNEX injection [The dosing schedule should be repeated on each day that ifosfamide is administered. When the dosage of ifosfamide is increased or decreased, the ratio of MESNEX to ifosfamide should be maintained.] | 240 mg/m^2 | – | –
MESNEX tablets | – | 480 mg/m^2 | 480 mg/m^2

The efficacy and safety of this ratio of intravenous and oral MESNEX has not been established as being effective for daily doses of ifosfamide higher than 2 g/m^2.

Patients who vomit within two hours of taking oral MESNEX should repeat the dose or receive intravenous MESNEX.

2.3 Monitoring for Hematuria

Maintain adequate hydration and sufficient urinary output, as required for ifosfamide treatment, and monitor urine for the presence of hematuria. If severe hematuria develops when MESNEX is given according to the recommended dosage schedule, dosage reductions or discontinuation of ifosfamide therapy may be required.

2.4 Preparation for Intravenous Administration and Stability

Preparation

Determine the volume of MESNEX injection for the intended dose.

Dilute the volume of MESNEX injection for the dose in any of the following fluids to obtain a final concentration of 20 mg/mL:

1. 5% Dextrose Injection, USP
2. 5% Dextrose and 0.2% Sodium Chloride Injection, USP
3. 5% Dextrose and 0.33% Sodium Chloride Injection, USP
4. 5% Dextrose and 0.45% Sodium Chloride Injection, USP
5. 0.9% Sodium Chloride Injection, USP
6. Lactated Ringer’s Injection, USP

Stability

The MESNEX injection multidose vials may be stored and used for up to 8 days after initial puncture.

Store diluted solutions at 25°C (77°F). Use diluted solutions within 24 hours.

Do not mix MESNEX injection with epirubicin, cyclophosphamide, cisplatin, carboplatin, and nitrogen mustard.

The benzyl alcohol contained in MESNEX injection vials can reduce the stability of ifosfamide. Ifosfamide and MESNEX may be mixed in the same bag provided the final concentration of ifosfamide does not exceed 50 mg/mL. Higher concentrations of ifosfamide may not be compatible with MESNEX and may reduce the stability of ifosfamide.

Parenteral drug products should be inspected visually for particulate matter and discoloration prior to administration whenever solution and container permit. Any solutions which are discolored, hazy, or contain visible particulate matter should not be used.

3 DOSAGE FORMS AND STRENGTHS

1. MESNEX (mesna) injection: 1 g Multidose Vial, 100 mg/mL
2. MESNEX (mesna) tablets: 400 mg film-coated tablets with functional score

4 CONTRAINDICATIONS

MESNEX is contraindicated in patients known to be hypersensitive to mesna or to any of the excipients [see Warnings and Precautions (5.1)].

5 WARNINGS AND PRECAUTIONS

5.1 Hypersensitivity Reactions

MESNEX may cause systemic hypersensitivity reactions, including anaphylaxis. These reactions may include fever, cardiovascular symptoms (hypotension, tachycardia), acute renal impairment, hypoxia, respiratory distress, urticaria, angioedema, laboratory signs of disseminated intravascular coagulation, hematological abnormalities, increased liver enzymes, nausea, vomiting, arthralgia, and myalgia. These reactions may occur with the first exposure or after several months of exposure. Monitor for signs or symptoms. Discontinue MESNEX and provide supportive care.

5.2 Dermatologic Toxicity

Drug rash with eosinophilia and systemic symptoms and bullous and ulcerative skin and mucosal reactions, consistent with Stevens-Johnson syndrome or toxic epidermal necrolysis have occurred. MESNEX may cause skin and mucosal reactions characterized by urticaria, rash, erythema, pruritus, burning sensation, angioedema, periorbital edema, flushing and stomatitis. These reactions may occur with the first exposure or after several months of exposure. Discontinue MESNEX and provide supportive care.

5.3 Benzyl Alcohol Toxicity

Serious adverse reactions including fatal reactions and the “gasping syndrome” occurred in premature neonates and low-birth weight infants who received benzyl alcohol dosages of 99 to 234 mg/kg/day (blood levels of benzyl alcohol were 0.61 to 1.378 mmol/L). Symptoms associated with “gasping syndrome” and other potential adverse reactions include gradual neurological deterioration, seizures, intracranial hemorrhage, hematological abnormalities, skin breakdown, hepatic and renal failure, hypotension, bradycardia, and cardiovascular collapse. Premature neonates and low-birth weight infants may be more likely to develop these reactions because they may be less able to metabolize benzyl alcohol. The minimum amount of benzyl alcohol at which toxicity may occur is not known. MESNEX injection contains 10.4 mg/mL of the preservative benzyl alcohol. Avoid use of MESNEX injection in premature neonates and low-birth weight infants. MESNEX tablets do not contain benzyl alcohol [see Use in Specific Populations (8.4)].

5.4 Laboratory Test Interferences

False-Positive Urine Tests for Ketone Bodies

A false positive test for urinary ketones may arise in patients treated with MESNEX when using nitroprusside sodium-based urine tests (including dipstick tests). The addition of glacial acetic acid can be used to differentiate between a false positive result (cherry-red color that fades) and a true positive result (red-violet color that intensifies).

False-Negative Tests for Enzymatic CPK Activity

MESNEX may interfere with enzymatic creatinine phosphokinase (CPK) activity tests that use a thiol compound (e.g., N-acetylcysteine) for CPK reactiviation. This may result in a falsely low CPK level.

False-Positive Tests for Ascorbic Acid

MESNEX may cause false-positive reactions in Tillman’s reagent-based urine screening tests for ascorbic acid.

5.5 Use in Patients with a History of Adverse Reactions to Thiol Compounds

MESNEX is a thiol compound, i.e., a sulfhydryl (SH) group-containing organic compound. Hypersensitivity reactions to mesna and to amifostine, another thiol compound, have been reported. It is not clear whether patients who experienced an adverse reaction to a thiol compound are at increased risk for a hypersensitivity reaction to MESNEX.

6 ADVERSE REACTIONS

The following are discussed in more detail in other sections of the labeling.

1. Hypersensitivity Reactions [see Warnings and Precautions (5.1)]
2. Dermatological Toxicity [see Warnings and Precautions (5.2)]
3. Benzyl Alcohol Toxicity [see Warnings and Precautions (5.3)]
4. Laboratory Test Interferences [see Warnings and Precautions (5.4)]
5. Use in Patients with a History of Adverse Reactions to Thiol Compounds [see Warnings and Precautions (5.5)]

6.1 Clinical Trials Experience

Because clinical trials are conducted under widely varying conditions, adverse reaction rates observed in the clinical trials of a drug cannot be directly compared to rates in the clinical trials of another drug and may not reflect the rates observed in practice.

MESNEX adverse reaction data are available from four Phase 1 studies in which single intravenous doses of 600-1200 mg MESNEX injection without concurrent chemotherapy were administered to a total of 53 healthy volunteers and single oral doses of 600-2400 mg of MESNEX tablets were administered to a total of 82 healthy volunteers. The most frequently reported side effects (observed in two or more healthy volunteers) for healthy volunteers receiving single doses of MESNEX injection alone were headache, injection site reactions, flushing, dizziness, nausea, vomiting, somnolence, diarrhea, anorexia, fever, pharyngitis, hyperesthesia, influenza-like symptoms, and coughing. In two Phase 1 multiple-dose studies where healthy volunteers received MESNEX tablets alone or intravenous MESNEX followed by repeated doses of MESNEX tablets, flatulence and rhinitis were reported. In addition, constipation was reported by healthy volunteers who had received repeated doses of intravenous MESNEX.

Additional adverse reactions in healthy volunteers receiving MESNEX alone included injection site reactions, abdominal pain/colic, epigastric pain/burning, mucosal irritation, lightheadedness, back pain, arthralgia, myalgia, conjunctivitis, nasal congestion, rigors, paresthesia, photophobia, fatigue, lymphadenopathy, extremity pain, malaise, chest pain, dysuria, pleuritic pain, dry mouth, dyspnea, and hyperhidrosis. In healthy volunteers, MESNEX was commonly associated with a rapid (within 24 hours) decrease in lymphocyte count, which was generally reversible within one week of administration.

Because MESNEX is used in combination with ifosfamide or ifosfamide-containing chemotherapy regimens, it is difficult to distinguish the adverse reactions which may be due to MESNEX from those caused by the concomitantly administered cytotoxic agents.

Adverse reactions reasonably associated with MESNEX administered intravenously and orally in four controlled studies in which patients received ifosfamide or ifosfamide-containing regimens are presented in Table 3.

Table 3: Adverse Reactions in ≥5% of Patients Receiving MESNEX in combination with Ifosfamide-containing Regimens
MESNEX Regimen | Intravenous-Intravenous-Intravenous [Intravenous dosing of ifosfamide and MESNEX followed by either intravenous or oral doses of MESNEX according to the applicable dosage schedule [see Dosage and Administration (2)].] | Intravenous-Oral-Oral
N exposed | 119 (100.0%) | 119 (100%)
Incidence of AEs | 101 (84.9%) | 106 (89.1%)
Nausea | 65 (54.6) | 64 (53.8)
Vomiting | 35 (29.4) | 45 (37.8)
Constipation | 28 (23.5) | 21 (17.6)
Leukopenia | 25 (21.0) | 21 (17.6)
Fatigue | 24 (20.2) | 24 (20.2)
Fever | 24 (20.2) | 18 (15.1)
Anorexia | 21 (17.6) | 19 (16.0)
Thrombocytopenia | 21 (17.6) | 16 (13.4)
Anemia | 20 (16.8) | 21 (17.6)
Granulocytopenia | 16 (13.4) | 15 (12.6)
Asthenia | 15 (12.6) | 21 (17.6)
Abdominal Pain | 14 (11.8) | 18 (15.1)
Alopecia | 12 (10.1) | 13 (10.9)
Dyspnea | 11 (9.2) | 11 (9.2)
Chest Pain | 10 (8.4) | 11 (9.2)
Hypokalemia | 10 (8.4) | 11 (9.2)
Diarrhea | 9 (7.6) | 17 (14.3)
Dizziness | 9 (7.6) | 5 (4.2)
Headache | 9 (7.6) | 13 (10.9)
Pain | 9 (7.6) | 10 (8.4)
Sweating Increased | 9 (7.6) | 2 (1.7)
Back Pain | 8 (6.7) | 6 (5.0)
Hematuria | 8 (6.7) | 7 (5.9)
Injection Site Reaction | 8 (6.7) | 10 (8.4)
Edema | 8 (6.7) | 9 (7.6)
Edema Peripheral | 8 (6.7) | 8 (6.7)
Somnolence | 8 (6.7) | 12 (10.1)
Anxiety | 7 (5.9) | 4 (3.4)
Confusion | 7 (5.9) | 6 (5.0)
Face Edema | 6 (5.0) | 5 (4.2)
Insomnia | 6 (5.0) | 11 (9.2)
Coughing | 5 (4.2) | 10 (8.4)
Dyspepsia | 4 (3.4) | 6 (5.0)
Hypotension | 4 (3.4) | 6 (5.0)
Pallor | 4 (3.4) | 6 (5.0)
Dehydration | 3 (2.5) | 7 (5.9)
Pneumonia | 2 (1.7) | 8 (6.7)
Tachycardia | 1 (0.8) | 7 (5.9)
Flushing | 1 (0.8) | 6 (5.0)

6.2 Postmarketing Experience

The following adverse reactions have been reported in the postmarketing experience of patients receiving MESNEX in combination with ifosfamide or similar drugs, making it difficult to distinguish the adverse reactions which may be due to MESNEX from those caused by the concomitantly administered cytotoxic agents. Because these reactions are reported from a population of unknown size, precise estimates of frequency cannot be made.

Cardiovascular: Hypertension

Gastrointestinal: Dysgeusia

Hepatobiliary: Hepatitis

Nervous System: Convulsion

Respiratory: Hemoptysis

7 DRUG INTERACTIONS

No clinical drug interaction studies have been conducted with MESNEX.

8 USE IN SPECIFIC POPULATIONS

8.1 Pregnancy

Risk Summary

MESNEX is used in combination with ifosfamide or other cytotoxic agents. Ifosfamide can cause fetal harm when administered to a pregnant woman. Refer to the ifosfamide prescribing information for more information on use during pregnancy.

MESNEX injection contains the preservative benzyl alcohol. Because benzyl alcohol is rapidly metabolized by a pregnant woman, benzyl alcohol exposure in the fetus is unlikely [see Warnings and Precautions (5.3) and Use in Specific Populations (8.4)].

The estimated background risk of major birth defects and miscarriage for the indicated populations are unknown. All pregnancies have a background risk of birth defect, loss, or other adverse outcomes. In the U.S. general population, the estimated background risk of major birth defects and miscarriage in clinically recognized pregnancies is 2-4% and 15-20%, respectively.

Data

Animal Data

MESNEX is used in combination with ifosfamide or other cytotoxic agents. Ifosfamide can cause fetal harm including embryo-fetal lethality. Refer to the ifosfamide prescribing information for more information on use during pregnancy.

In embryo-fetal development studies, oral administration of mesna to pregnant rats (500, 1000, 1500, and 2000 mg/kg) and rabbits (500 and 1000 mg/kg) during the period of organogenesis revealed no adverse developmental outcomes at doses approximately 10 times the maximum recommended total daily human equivalent dose based on body surface area.

8.2 Lactation

Risk Summary

MESNEX is used in combination with ifosfamide or other cytotoxic agents. Ifosfamide is excreted in breast milk. Refer to the ifosfamide prescribing information for more information on use during lactation. There are no data on the presence of mesna in human or animal milk, the effect on the breastfed child, or the effect on milk production.

MESNEX injection contains the preservative benzyl alcohol. Because benzyl alcohol is rapidly metabolized by a lactating woman, benzyl alcohol exposure in the breastfed infant is unlikely. However, adverse reactions have occurred in premature neonates and low birth weight infants who received intravenously administered benzyl alcohol-containing drugs [see Warnings and Precautions (5.3) and Use in Specific Populations (8.4)].

Because of the potential for serious adverse reactions in a breastfed child, advise lactating women not to breastfeed during treatment and for 1 week after the last dose of MESNEX or ifosfamide.

8.3 Females and Males of Reproductive Potential

MESNEX is used in combination with ifosfamide or other cytotoxic agents. Ifosfamide can cause fetal harm when administered to a pregnant woman. Refer to the ifosfamide prescribing information for more information on contraception and effects on fertility.

Pregnancy Testing

Verify the pregnancy status of females of reproductive potential prior to initiation of MESNEX in combination with ifosfamide.

Contraception

Females

Advise females of reproductive potential to use effective contraception during treatment with MESNEX in combination with ifosfamide and for 6 months after the last dose.

Males

Advise males with female partners of reproductive potential to use effective contraception during treatment with MESNEX in combination with ifosfamide and for 3 months after the last dose.

8.4 Pediatric Use

MESNEX injection contains the preservative benzyl alcohol which has been associated with serious adverse reactions and death when administered intravenously to premature neonates and low birth weight infants. Avoid use of MESNEX injection in premature neonates and low-birth weight infants [see Warnings and Precautions (5.3)].

8.5 Geriatric Use

Clinical studies of MESNEX did not include sufficient numbers of subjects aged 65 and over to determine whether they respond differently from younger subjects. In general, dose selection for an elderly patient should be cautious, reflecting the greater frequency of decreased hepatic, renal, or cardiac function, and of concomitant disease or other drug therapy. The ratio of ifosfamide to MESNEX should remain unchanged.

8.6 Use in Patients with Renal Impairment

No clinical studies were conducted to evaluate the effect of renal impairment on the pharmacokinetics of MESNEX.

8.7 Use in Patients with Hepatic Impairment

No clinical studies were conducted to evaluate the effect of hepatic impairment on the pharmacokinetics of MESNEX.

10 OVERDOSAGE

There is no known antidote for MESNEX.

In a clinical trial, 11 patients received intravenous MESNEX 10 mg/kg to 66 mg/kg per day for 3 to 5 days. Patients also received ifosfamide or cyclophosphamide. Adverse reactions included nausea, vomiting, diarrhea and fever. An increased rate of these adverse reactions has also been found in oxazaphosphorine-treated patients receiving ≥80 mg MESNEX per kg per day intravenously compared with patients receiving lower doses or hydration treatment only.

Postmarketing, administration of 4.5 g to 6.9 g of MESNEX resulted in hypersensitivity reactions including mild hypotension, shortness of breath, asthma exacerbation, rash, and flushing.

11 DESCRIPTION

MESNEX (mesna) is a detoxifying agent to inhibit the hemorrhagic cystitis induced by ifosfamide. The active ingredient, mesna, is a synthetic sulfhydryl compound designated as sodium-2-mercaptoethane sulfonate with a molecular formula of C2H5NaO3S2 and a molecular weight of 164.18. Its structural formula is as follows:

HS–CH2–CH2SO3–Na^+

MESNEX injection is a sterile, nonpyrogenic, aqueous solution of clear and colorless appearance in clear glass multidose vials for intravenous administration. MESNEX injection contains 100 mg/mL mesna, 0.25 mg/mL edetate disodium and sodium hydroxide for pH adjustment. MESNEX injection multidose vials also contain 10.4 mg/mL of benzyl alcohol as a preservative. The solution has a pH range of 7.5-8.5.

MESNEX tablets are white, oblong, scored biconvex film-coated tablets with the imprint M4. They contain 400 mg mesna. The excipients are calcium phosphate, cornstarch, hydroxypropylmethylcellulose, lactose, magnesium stearate, microcrystalline cellulose, polyethylene glycol, povidone, simethicone, and titanium dioxide.

12 CLINICAL PHARMACOLOGY

12.1 Mechanism of Action

Mesna reacts chemically with the urotoxic ifosfamide metabolites, acrolein and 4-hydroxy-ifosfamide, resulting in their detoxification. The first step in the detoxification process is the binding of mesna to 4-hydroxy-ifosfamide forming a non-urotoxic 4-sulfoethylthioifosfamide. Mesna also binds to the double bonds of acrolein and to other urotoxic metabolites and inhibits their effects on the bladder.

12.3 Pharmacokinetics

Absorption

Following oral administration, peak plasma concentrations were reached within 1.5 to 4 hours and 3 to 7 hours for free mesna and total mesna (mesna plus dimesna and mixed disulfides), respectively. Oral bioavailability averaged 58% (range 45 to 71%) for free mesna and 89% (range 74 to 104%) for total mesna based on plasma AUC data from 8 healthy volunteers who received 1200 mg oral or intravenous doses.

Food does not affect the urinary availability of orally administered MESNEX.

Distribution

Mean apparent volume of distribution (Vd) for mesna is 0.652 ± 0.242 L/kg after intravenous administration which suggests distribution to total body water (plasma, extracellular fluid, and intracellular water).

Metabolism

Analogous to the physiological cysteine-cystine system, mesna is rapidly oxidized to its major metabolite, mesna disulfide (dimesna). Plasma concentrations of mesna exceed those of dimesna after oral or intravenous administration.

Excretion

Following intravenous administration of a single 800 mg dose, approximately 32% and 33% of the administered dose was eliminated in the urine in 24 hours as mesna and dimesna, respectively. Mean plasma elimination half-lives of mesna and dimesna are 0.36 hours and 1.17 hours, respectively. Mesna has a plasma clearance of 1.23 L/h/kg.

13 NONCLINICAL TOXICOLOGY

13.1 Carcinogenesis, Mutagenesis, Impairment of Fertility

No long-term studies in animals have been performed to evaluate the carcinogenic potential of mesna.

Mesna was not genotoxic in the in vitro Ames bacterial mutagenicity assay, the in vitro mammalian lymphocyte chromosomal aberration assay or the in vivo mouse micronucleus assay.

No studies on male or female fertility were conducted. No signs of male or female reproductive organ toxicity were seen in 6-month oral rat studies (≤ 2000 mg/kg/day) or 29-week oral dog studies (520 mg/kg/day) at doses approximately 10-fold higher than the maximum recommended human dose on a body surface area basis.

14 CLINICAL STUDIES

14.1 Intravenous MESNEX

Hemorrhagic cystitis produced by ifosfamide is dose dependent (Table 4). At a dose of 1.2 g/m^2 ifosfamide administered daily for 5 days, 16 to 26% of the patients who received conventional uroprophylaxis (high fluid intake, alkalinization of the urine, and the administration of diuretics) developed hematuria (>50 RBC per hpf or macrohematuria) (Studies 1, 2, and 3). In contrast, none of the patients who received mesna injection together with this dose of ifosfamide developed hematuria (Studies 3 and 4). In two randomized studies, (Studies 5 and 6), higher doses of ifosfamide, from 2 g/m^2 to 4 g/m^2 administered for 3 to 5 days, produced hematuria in 31 to 100% of the patients. When MESNEX was administered together with these doses of ifosfamide, the incidence of hematuria was less than 7%.

Table 4. Percent of MESNEX Patients Developing Hematuria (≥50 RBC/hpf or macrohematuria)
Study | Conventional Uroprophylaxis (number of patients) | Standard MESNEX (mesna) Intravenous Regimen (number of patients)
Uncontrolled Studies [Ifosfamide dose 1.2 g/m^2 d x 5]
Study 1 | 16% (7/44) | -
Study 2 | 26% (11/43) | -
Study 3 | 18% (7/38) | 0% (0/21)
Study 4 | - | 0% (0/32)
Controlled Studies [Ifosfamide dose 2 g/m^2 to 4 g/m^2 d x 3 to 5]
Study 5 | 31% (14/46) | 6% (3/46)
Study 6 | 100% (7/7) | 0% (0/8)

14.2 Oral MESNEX

Clinical studies comparing recommended intravenous and oral MESNEX dosing regimens demonstrated incidences of grade 3 to 4 hematuria of <5%. Study 7 was an open label, randomized, two-way crossover study comparing three intravenous doses with an initial intravenous dose followed by two oral doses of MESNEX in patients with cancer treated with ifosfamide at a dose of 1.2 g/m^2 to 2.0 g/m^2 for 3 to 5 days. Study 8 was a randomized, multicenter study in cancer patients receiving ifosfamide at 2.0 g/m^2 for 5 days. In both studies, development of grade 3 or 4 hematuria was the primary efficacy endpoint. The percent of patients developing hematuria in each of these studies is presented in Table 5.

Table 5. Percent of MESNEX Patients Developing Grade 3 or 4 Hematuria
 | MESNEX Dosing Regimen
Study | Standard Intravenous Regimen; (number of patients) | Intravenous + Oral Regimen; (number of patients)
Study 7 | 0% (0/30) | 3.6% (1/28)
Study 8 | 3.7% (1/27) | 4.3% (1/23)

16 HOW SUPPLIED/STORAGE AND HANDLING

MESNEX (mesna) injection 100 mg/mL

1. NDC 0338-1305-01
  1 g Multidose Vial, Box of 1 vial of 10 mL
2. NDC 0338-1305-03
  1 g Multidose Vial, Box of 10 vials of 10 mL
Store at 20°C to 25°C (68°F to 77°F), excursions permitted to 15°C to 30°C (59°F to 86°F) [see USP Controlled Room Temperature]

If MESNEX is co-administered with ifosfamide, refer to the ifosfamide prescribing information for safe handling instructions.

MESNEX (mesna) tablets

1. NDC 67108-3565-9
  400 mg scored tablets packaged in box of 10 tablets
Store at 20°C to 25°C (68°F to 77°F), excursions permitted to 15°C to 30°C (59°F to 86°F) [see USP Controlled Room Temperature]

17 PATIENT COUNSELING INFORMATION

See FDA-approved patient labeling (Patient Information).

Hypersensitivity

1. Advise the patient to discontinue MESNEX and seek immediate medical attention if any signs or symptoms of a hypersensitivity reaction, including systemic anaphylactic reactions occur [see Warnings and Precautions (5.1)].

Dosing Instructions

1. Advise the patient to take MESNEX at the exact time and in the exact amount as prescribed. Advise the patient to contact their healthcare provider if they vomit within 2 hours of taking oral MESNEX, or if they miss a dose of oral MESNEX [see Dosage and Administration (2.2)].

Hemorrhagic Cystitis

1. MESNEX does not prevent hemorrhagic cystitis in all patients nor does it prevent or alleviate any of the other adverse reactions or toxicities associated with ifosfamide. Advise the patient to report to their healthcare provider if his/her urine has turned a pink or red color [see Dosage and Administration (2.3)].
2. Advise the patient to drink 1 to 2 liters of fluid each day during MESNEX therapy [see Dosage and Administration (2.3)].

Dermatologic Toxicity

1. Advise the patient that Stevens-Johnson syndrome, toxic epidermal necrolysis, and drug rash with eosinophilia and systemic symptoms and bullous and ulcerative skin and mucosal reactions have occurred with MESNEX. Advise the patient to report to their healthcare provider if signs and symptoms of these syndromes occur [see Warnings and Precautions (5.2)].

Benzyl Alcohol Toxicity

1. Advise patients that serious adverse reactions are associated with the benzyl alcohol found in MESNEX and other medications in premature neonates and low-birth weight infants [see Warnings and Precautions (5.3) and Use in Specific Populations (8.4)].

Embryo-Fetal Toxicity

1. MESNEX is used in combination with ifosfamide. Ifosfamide or other cytotoxic agents can cause fetal harm when administered to a pregnant woman. Inform female patients of the risk to a fetus and potential loss of the pregnancy. Advise females to inform their healthcare provider if they are pregnant or become pregnant [see Use in Specific Populations (8.1)].

Contraception

1. Advise females of reproductive potential to use effective contraception during treatment with MESNEX in combination with ifosamide and for 6 months after the last dose [see Use in Specific Populations (8.3)].
2. Advise male patients with female partners of reproductive potential to use effective contraception during treatment with MESNEX in combination with ifosamide and for 3 months after the last dose [see Use in Specific Populations (8.3)].

Lactation

1. Advise lactating women not to breastfeed during treatment with MESNEX or ifosfamide and for 1 week after the last dose [see Use in Specific Populations (8.2)].

Baxter Logo
MESNEX (mesna) injection manufactured by:

MESNEX (mesna) tablets manufactured for:

Baxter Healthcare Corporation
Deerfield, IL 60015 USA
For Product Inquiry 1800 ANA DRUG (1-800-262-3784)

Made in Germany

Baxter and Mesnex are registered trademarks of Baxter International Inc.

Material No. HA-30-01-811

Patient Information
MESNEX (MES-nex)
(mesna)
tablets

MESNEX (MES-nex)
(mesna)
injection

What is the most important information I should know about MESNEX?

MESNEX can cause serious allergic reactions and skin reactions. These serious reactions can happen the first time you are treated with MESNEX or after several months of treatment with MESNEX. Stop treatment with MESNEX and go to the nearest hospital emergency room right away if you develop any of the symptoms listed below:

- fever
- swelling of your face, lips, mouth, or tongue
- trouble breathing or wheezing
- itching
- burning
- skin rash or hives
- skin redness or swelling

- skin blisters or peeling
- feel lightheaded or faint
- feel like your heart is racing
- nausea
- vomiting
- joint or muscle aches
- mouth sores

See “What are the possible side effects of MESNEX?” for more information about side effects.

What is MESNEX?

MESNEX is a prescription medicine used to reduce the risk of inflammation and bleeding of the bladder (hemorrhagic cystitis) in people who receive ifosfamide (a medicine used to treat cancer).

MESNEX is not for use to reduce the risk of blood in the urine (hematuria) due to other medical conditions.

Do not take MESNEX tablets or receive MESNEX by intravenous (IV) infusion if you are allergic to mesna or any of the ingredients in MESNEX. See the end of this leaflet for a complete list of ingredients in MESNEX.

Before you take or receive MESNEX, tell your healthcare provider about all of your medical conditions, including if you:

- are allergic to any medicines
- are pregnant or plan to become pregnant.
Females who are able to become pregnant:
- Your healthcare provider will verify if you are pregnant or not before you start treatment with MESNEX and ifosfamide.
- You should use effective birth control (contraception) during treatment with MESNEX and ifosfamide and for 6 months after the last dose.
- Tell your healthcare provider if you become pregnant during treatment with MESNEX and ifosfamide.
Males with female partners who are able to become pregnant should use effective birth control during treatment with MESNEX and ifosfamide and for 3 months after the last dose.
You should also read the ifosfamide Prescribing Information for important pregnancy, contraception, and infertility information.
- are breastfeeding or plan to breastfeed. It is not known if MESNEX passes into your breast milk. Do not breastfeed during treatment and for 1 week after the last dose of MESNEX or ifosfamide.

Tell your healthcare provider about all the medicines you take, including prescription and over-the-counter medicines, vitamins, and herbal supplements.

How will I receive MESNEX?

- MESNEX is given on the same day that you receive ifosfamide.
- MESNEX can be given by an intravenous (IV) infusion into a vein or tablets taken by mouth.
- You will receive MESNEX in one of two ways:
- MESNEX intravenous (IV) infusion into a vein at the time you receive ifosfamide and 4 and 8 hours after you receive ifosfamide, OR
- MESNEX intravenous (IV) infusion into a vein at the time you receive ifosfamide and MESNEX tablets taken by mouth 2 and 6 hours after you receive ifosfamide.
- Take MESNEX tablets at the exact times and the exact dose your healthcare provider tells you to take it.
- During treatment with MESNEX intravenous (IV) infusion or MESNEX tablets, you should drink 4 to 8 cups of liquid (1 to 2 liters) each day.
- Tell your healthcare provider if you:
- vomit within 2 hours of taking MESNEX tablets by mouth
- miss a dose of MESNEX tablets
- have pink or red colored urine

What are the possible side effects of MESNEX?

MESNEX may cause serious side effects, including:

See “What is the most important information I should know about MESNEX?”

- MESNEX that is given by intravenous (IV) infusion contains the preservative benzyl alcohol. Benzyl alcohol has been shown to cause serious side effects and death in premature newborns and low-birth weight babies. Avoid use of MESNEX injection in premature newborns and low birth weight infants. MESNEX tablets do not contain benzyl alcohol.

The most common side effects of MESNEX when given with ifosfamide include:

- nausea
- vomiting
- constipation
- decreased white blood cell count
- tiredness
- fever
- decreased appetite
- decreased platelet count

- decreased red blood cell count
- diarrhea
- weakness
- stomach (abdomen) pain
- headache
- hair loss
- sleepiness

These are not all the possible side effects of MESNEX.

Call your doctor for medical advice about side effects. You may report side effects to FDA at 1-800-FDA-1088.

How should I store MESNEX tablets?

- Store MESNEX tablets at room temperature between 68°F to 77°F (20°C to 25°C).

Keep MESNEX and all medicines out of the reach of children.

General information about the safe and effective use of MESNEX.

Medicines are sometimes prescribed for purposes other than those listed in a Patient Information leaflet. Do not use MESNEX for a condition for which it was not prescribed. Do not give MESNEX to other people, even if they have the same symptoms that you have. It may harm them. You can ask your pharmacist or healthcare provider for information about MESNEX that is written for health professionals.

What are the ingredients in MESNEX?

Active ingredient: mesna

Inactive ingredients:

MESNEX injection: edetate disodium, sodium hydroxide, and benzyl alcohol as a preservative.

MESNEX tablets: calcium phosphate, cornstarch, hydroxypropylmethylcellulose, lactose, magnesium stearate, microcrystalline cellulose, polyethylene glycol, povidone, simethicone, and titanium dioxide.

Manufactured by: Baxter Healthcare Corporation, Deerfield, IL 60015 USA

Made in Germany

Baxter and Mesnex are registered trademarks of Baxter International Inc.

For more information, call 1-800-262-3784.

This Patient Information has been approved by the U.S. Food and Drug Administration. Revised: 12 2018

PACKAGE LABEL - PRINCIPAL DISPLAY PANEL

Container Label 400 mg Tablets

Container Label 400 mg Tablets

List 3565-9

Rx only

400 mg

Mesnex®
(mesna) Tablets

Baxter Healthcare
Corporation
460-656-00

Lot-number/Expires:

JMXXXA JJJJ - MM

Carton Label 400 mg Tablets

10 400 mg Tablets

NDC 67108-3565-9

400 mg

Mesnex®
(mesna) Tablets

Rx only

Each tablet contains 400 mg mesna.
Store at 20°-25°C (68°-77°F), excursions permitted to 15°-30°C (59°-86°F)
[see USP Controlled Room Temperature].

For ORAL ADMINISTRATION

Dosage: See package insert for directions for use. Should not be prescribed without thorough
knowledge of dose, indications, and toxicology as contained in the accompanying literature.

Manufactured for :
Baxter Logo
Baxter Healthcare Corporation
Deerfield, IL 60015

Barcode
N3 6710835659 1

C
926

10 400 mg Tablets

400
mg

Mesnex®
(mesna) Tablets

NDC 67108-3565-9

HA-80-02-274
USA

10 400 mg Tablets

400
mg

Mesnex®
(mesna) Tablets

NDC 67108-3565-9

2640B4050

Barcode

10 400 mg Tablets

400
mg

Mesnex®
(mesna) Tablets

NDC 67108-3565-9

Rx only

Each tablet contains 400 mg mesna.
Store at 20°-25°C (68°-77°F), excursions permitted to 15°-30°C (59°-86°F)
[see USP Controlled Room Temperature].

For ORAL ADMINISTRATION

Dosage: See package insert for directions for use. Should not be prescribed without thorough
knowledge of dose, indications, and toxicology as contained in accompanying literature.

Manufactured for:
Baxter Logo
Baxter Healthcare Corporation
Deerfield, IL 60015

10 400 mg Tablets

400
mg

Mesnex®
(mesna) Tablets

NDC 67108-3565-9

51741274